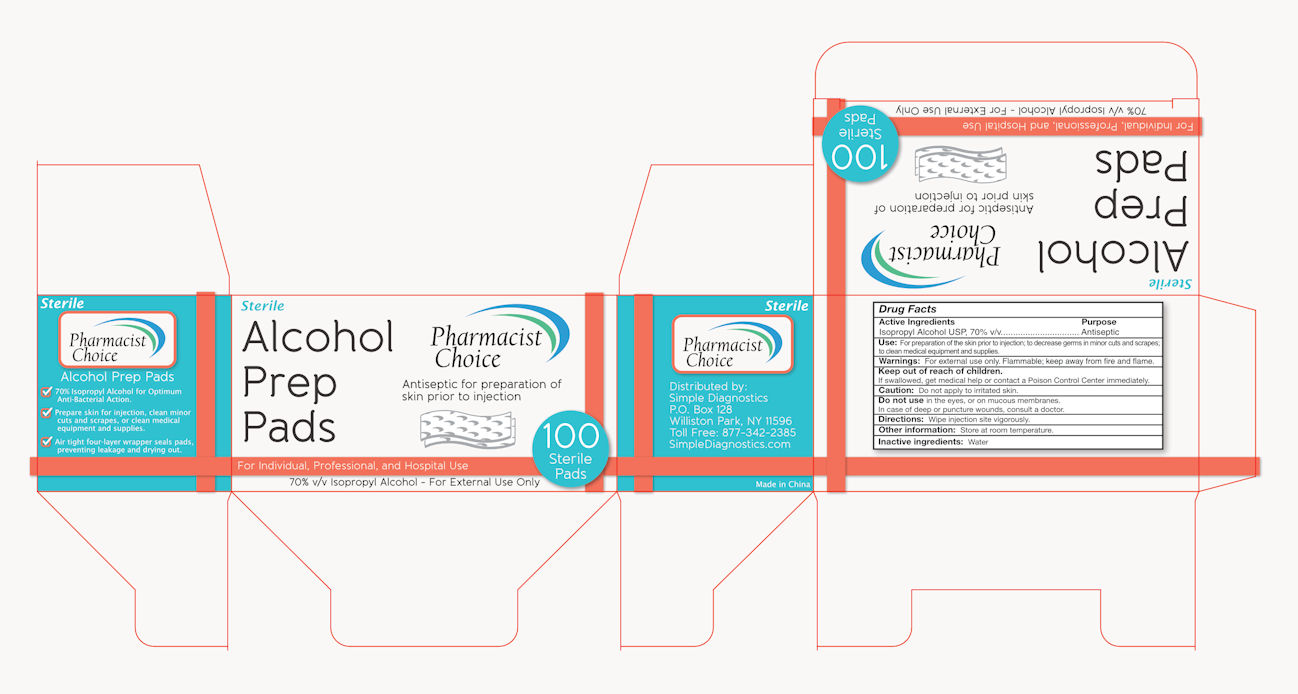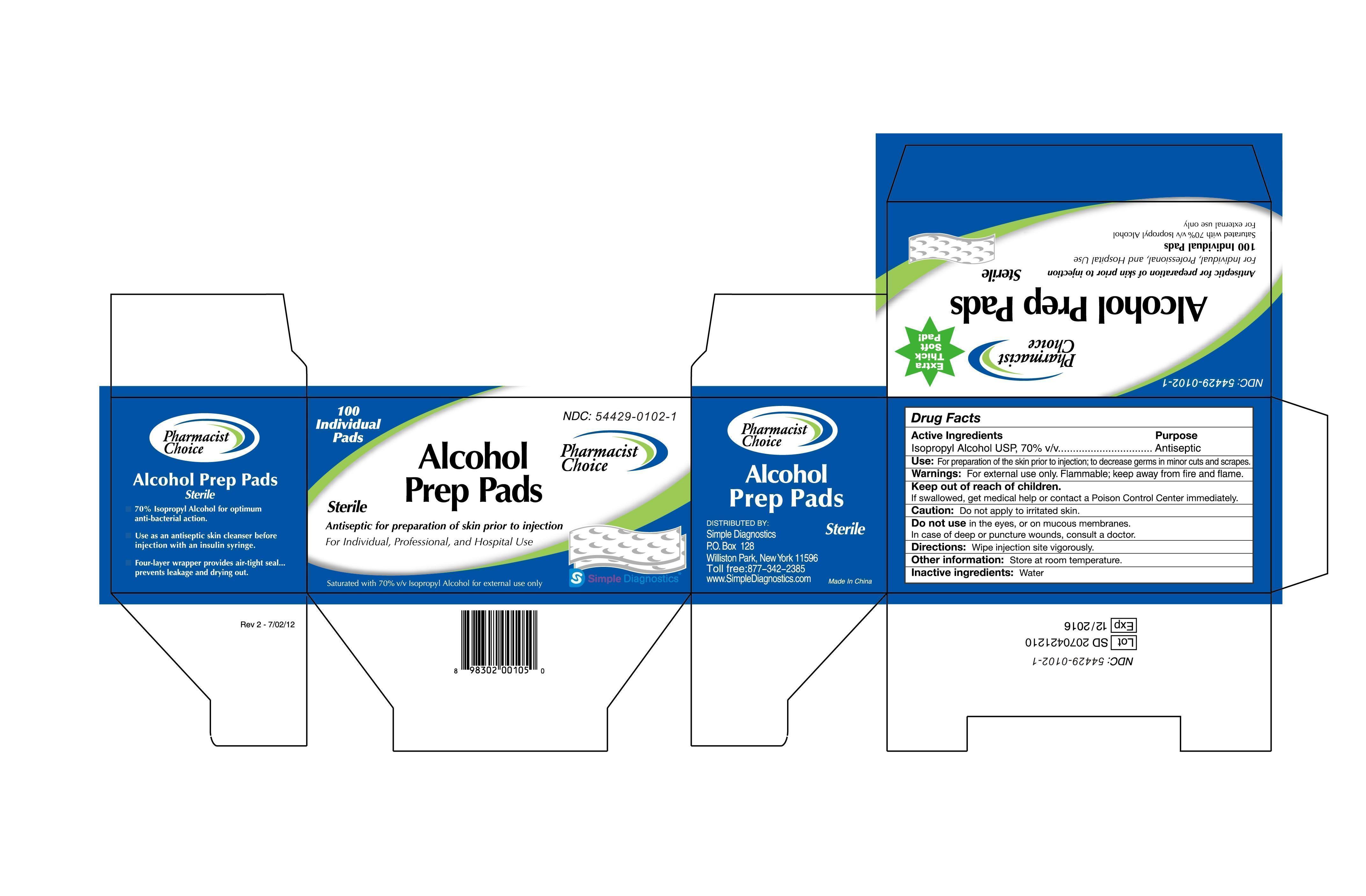 DRUG LABEL: PHARMACIST CHOICE ALCOHOL STERILE PREP PAD
NDC: 62379-005 | Form: SWAB
Manufacturer: Simple Diagnostics
Category: otc | Type: HUMAN OTC DRUG LABEL
Date: 20250204

ACTIVE INGREDIENTS: ISOPROPYL ALCOHOL 0.7 mL/1 mL
INACTIVE INGREDIENTS: WATER

PHARMACIST CHOICE ALCOHOL PREP PADS

Active Ingredients

Isopropyl Alcohol USP, 70% v/v

Purpose

Antiseptic

Keep out of children

If swallowed, get medical help or contact a Poison Control Center immediately.

Use

For preparation of skin prior to injection; to decrease germs in minor cuts and scrapes.

Warning

For external use only. Flammable, keep away from fire and flame.

Directions

Wipe injection site vigorously.

Inactive ingredients

Water

Drug Facts

Active Ingredients

Isopropyl Alcohol USP, 70% v/v

Purpose:

Antiseptic

Use: For preparation of skin prior to injection; to decrease germs in minor cuts and scrapes.

Warning: For external use only. Flammable, keep away from fire and flame.

Keep out of children.

If swallowed, get medical help or contact a Poison Control Center immediately.

Caution: Don’t apply to a irritated skin.

Don’t use in the eyes, or on mucous membranes.

In case of deep or puncture wounds, consult a doctor.

Directions: wipe injection site vigorously.

Other information: Store at room temperature.

Inactive ingredients: Water